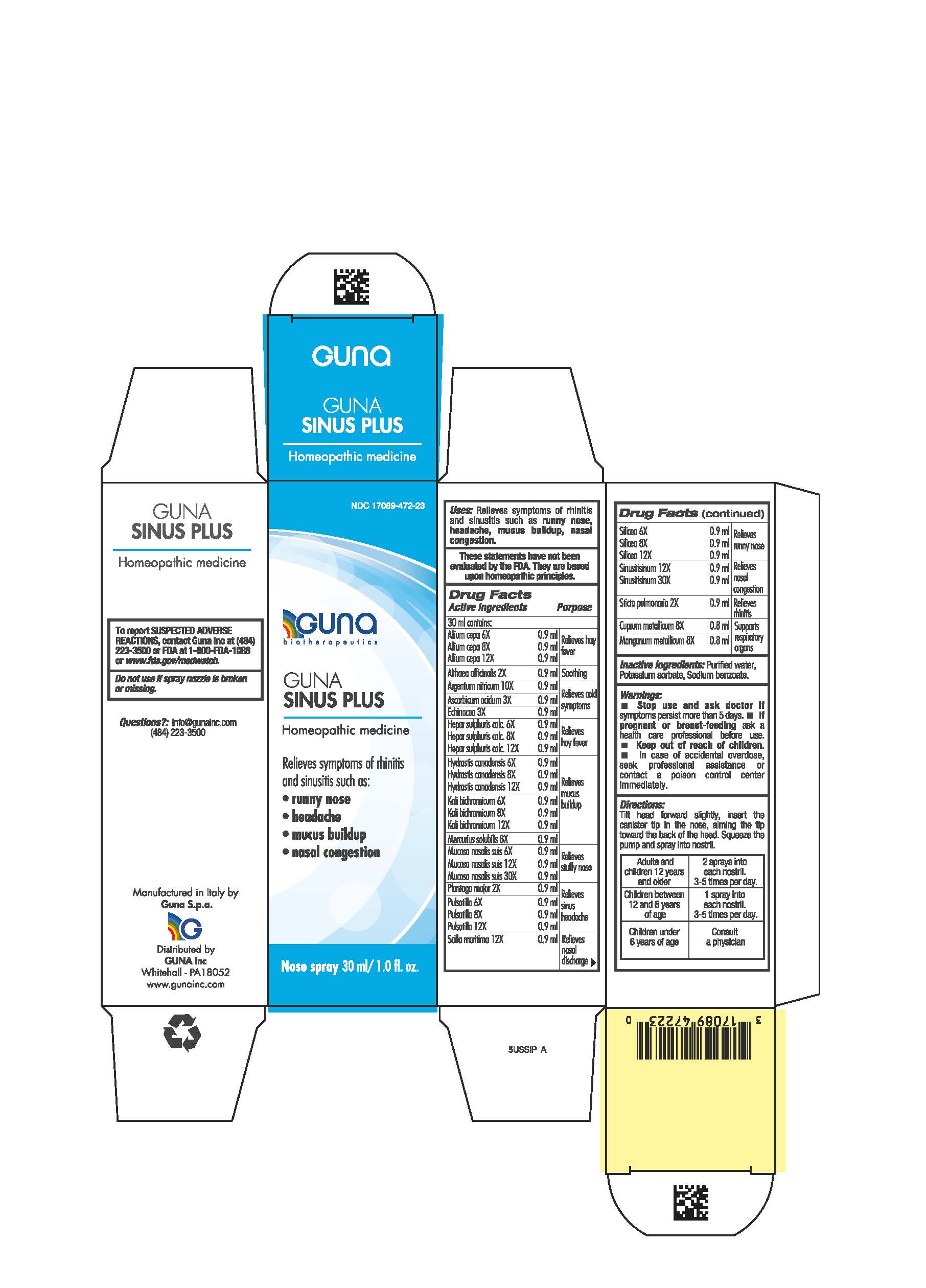 DRUG LABEL: GUNA SINUS PLUS
NDC: 17089-472 | Form: SPRAY
Manufacturer: Guna spa
Category: homeopathic | Type: HUMAN OTC DRUG LABEL
Date: 20210217

ACTIVE INGREDIENTS: ONION 6 [hp_X]/30 mL; ALTHAEA OFFICINALIS LEAF 2 [hp_X]/30 mL; SILVER NITRATE 10 [hp_X]/30 mL; ASCORBIC ACID 3 [hp_X]/30 mL; HYDRASTIS CANADENSIS WHOLE 6 [hp_X]/30 mL; LOBARIA PULMONARIA 2 [hp_X]/30 mL; COPPER 8 [hp_X]/30 mL; ECHINACEA ANGUSTIFOLIA 3 [hp_X]/30 mL; CALCIUM SULFIDE 6 [hp_X]/30 mL; POTASSIUM DICHROMATE 6 [hp_X]/30 mL; MANGANESE 8 [hp_X]/30 mL; MERCURIC SULFIDE 8 [hp_X]/30 mL; SUS SCROFA NASAL MUCOSA 6 [hp_X]/30 mL; PULSATILLA VULGARIS 6 [hp_X]/30 mL; SILICON DIOXIDE 6 [hp_X]/30 mL; SINUSITISINUM 12 [hp_X]/30 mL; PLANTAGO MAJOR WHOLE 2 [hp_X]/30 mL; DRIMIA MARITIMA BULB 12 [hp_X]/30 mL
INACTIVE INGREDIENTS: POTASSIUM SORBATE 0.03 mL/30 mL; SODIUM BENZOATE 0.03 mL/30 mL

GUNA SINUS PLUS

DIRECTIONS

Adults and children 12 years and older 2 sprays to each nostril, 3-5 times per day
Children between 12 years and 6 years of age 1 spray to each nostril, 3-5 times per day
Children under 6 years consult a physician

ACTIVE INGREDIENTS/PURPOSE

- ALLIUM CEPA 6X, 8X, 12X Relieves hay fever
- ALTHEA OFFICINALIS 2X Soothing
- ARGENTUM NITRICUM 10X Relieves cold symptoms
- ASCORBIC ACIDUM 3X Relieves cold symptoms
- ECHINACEA 3X Relieves cold symptoms
- HEPAR SULPHURIS CALCAREUM 6X, 8X, 12X Relieves hay fever
- HYDRASTIS CANADENSIS 6X, 8X, 12X Relieves mucus buildup
- KALI BICHROMICUM 6X, 8X, 12X Relieves mucus buildup
- MERCURIUS SOLUBILIS 8X Relieves mucus buildup
- MUCOSA NASALIS SUIS 6X, 12X, 30X Relieves stuffy nose
- PLANTAGO MAJOR 2X Relieves sinus headache
- PULSATILLA 6X, 8X, 12X Relieves sinus headache
- SCILLA MARITIMA 12X Relieves nasal discharge
- SILICEA 6X, 8X, 12X Relieves runny nose
- SINUSITISINUM 12X, 30X Relieves nasal congestion
- STICTA PULMONARIA 2X Relieves rhinitis
- CUPRUM METALLICUM 8X Supports respiratory organs
- MANGANUM METALLICUM 8X Supports respiratory organs

Directions:

tilt head forward slightly, insert the canister tip in the nose, aiming the tip toward the back of the head. Squeeze the pump and spray intro nostril.

Inactive ingredient:purified water, potassium sorbate, sodium benzoate.

QUESTIONS

Questions?: info@gunainc.com
Tel. (484) 223-3500

WARNINGS

Keep out of reach of children.

PREGNANCY

If pregnant or breast-feeding ask a health care profesisonal before use

WARNINGS

- Stop use and ask doctor if symptoms persist more than 5 days.
- If pregnant or breast-feeding ask a health professional before use.
- Keep out of reach of children. In case of overdose, seek professional assistance or contact a Poison Control Center immediately.

USES

Relieves symptoms of rhinitis and sinusitis such as:

- runny nose
- headache
- mucus buildup
- nasal congestion